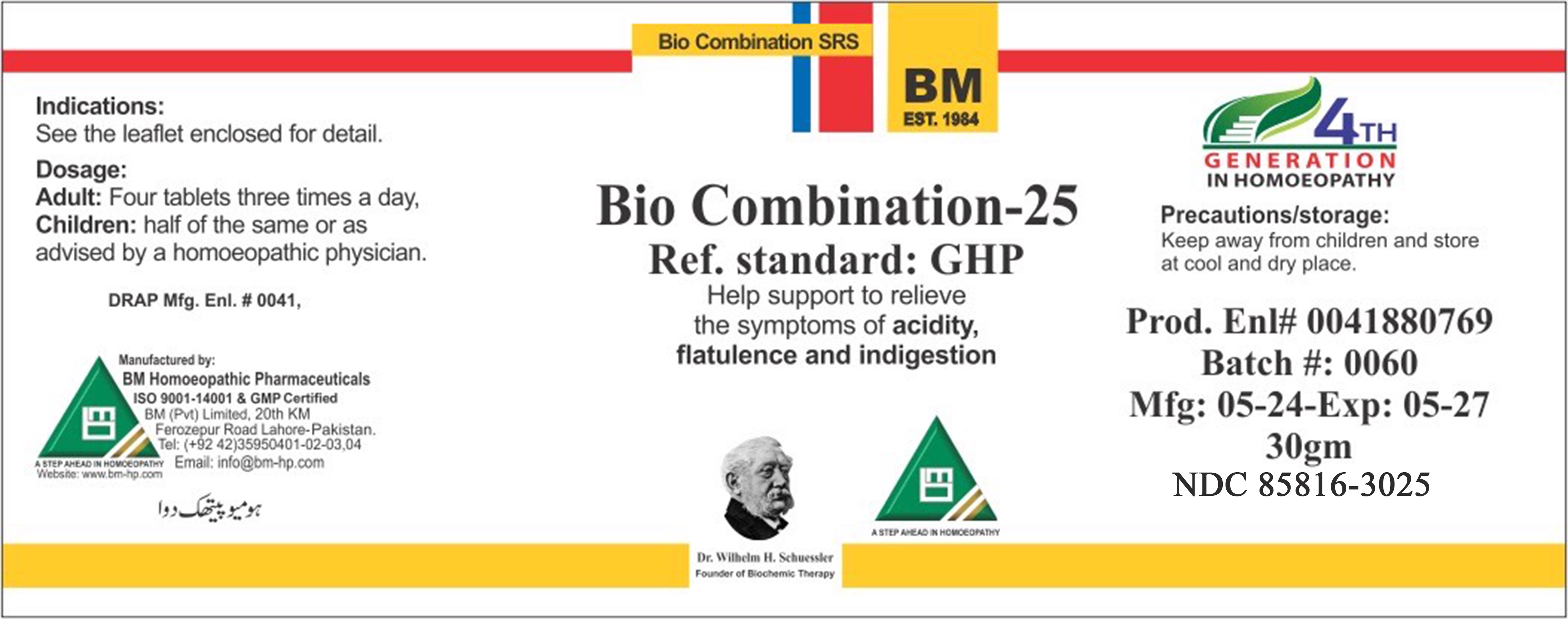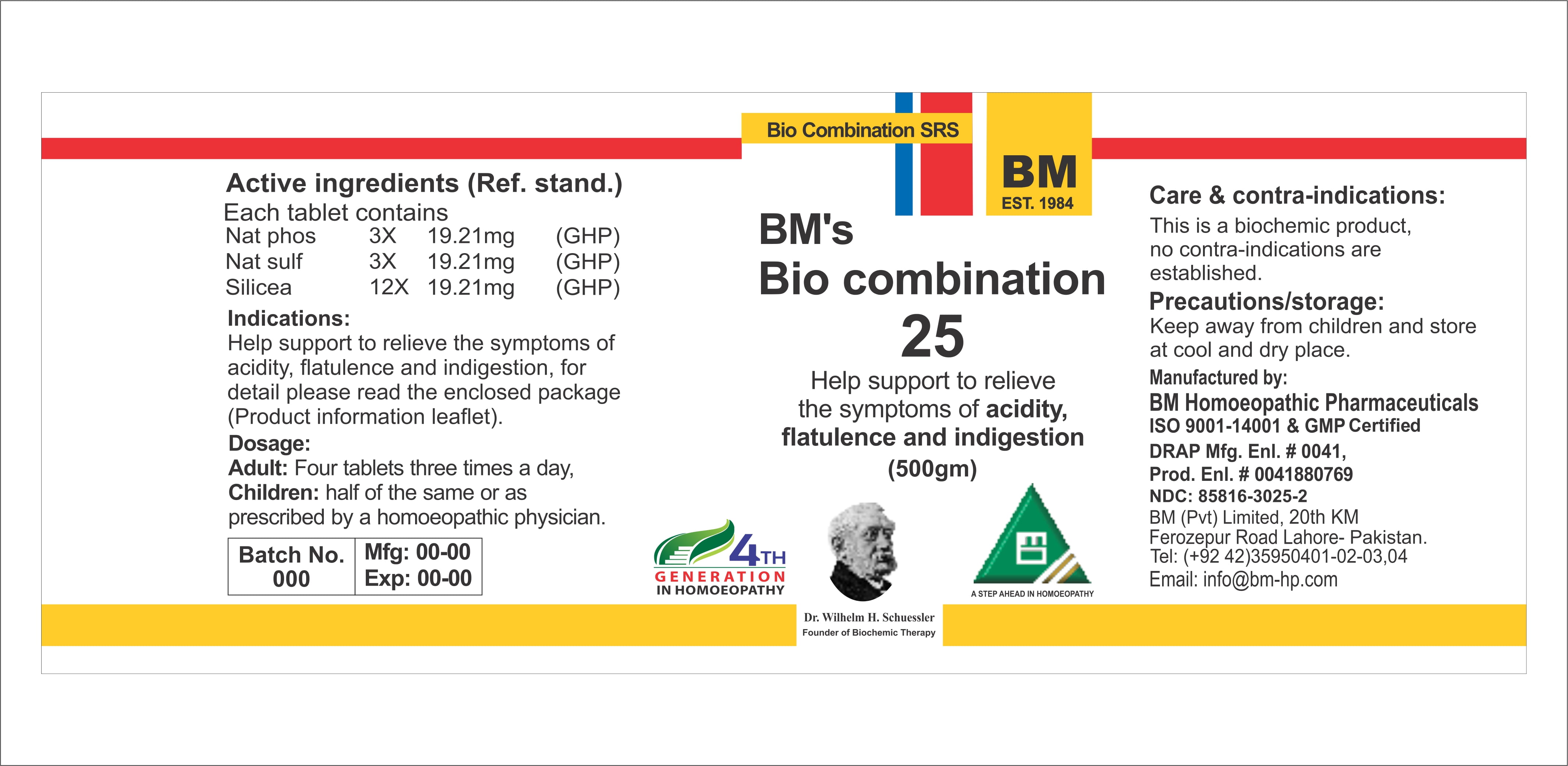 DRUG LABEL: BIO COM 25 ACIDITY
NDC: 85816-3025 | Form: GLOBULE
Manufacturer: BM Private Limited
Category: homeopathic | Type: HUMAN OTC DRUG LABEL
Date: 20260217

ACTIVE INGREDIENTS: SODIUM SULFATE 6 [hp_X]/1 g; SODIUM PHOSPHATE, DIBASIC, HEPTAHYDRATE 6 [hp_X]/1 g; SILICA 6 [hp_X]/1 g
INACTIVE INGREDIENTS: MAGNESIUM STEARATE 0.0208 g/1 g; LACTOSE, UNSPECIFIED FORM 0.978 g/1 g

HOMEOPATHIC REMEDY BIO COM 25 ACIDITY

Dosage:
Adults: Four tablets three times a day.
Children: half of the same or as advised by a homeopathic physician.

ACTIVE INGREDIENT

Nat phos, nat sulph, silicea

INACTIVE INGREDIENT

LACTOSE, MAGNESIUM STEARATE

INDICATIONS AND USAGE

See the enclosed detail for detail

PURPOSE

For detail, please read the enclosed package (product information leaflet)

KEEP OUT OF REACH OF CHILDREN

Precautions/storage:
Keep away from children and store at cool and dry place.

WARNINGS

Precautions/storage:
Keep away from children and store at cool and dry place.

package 1: Package 2